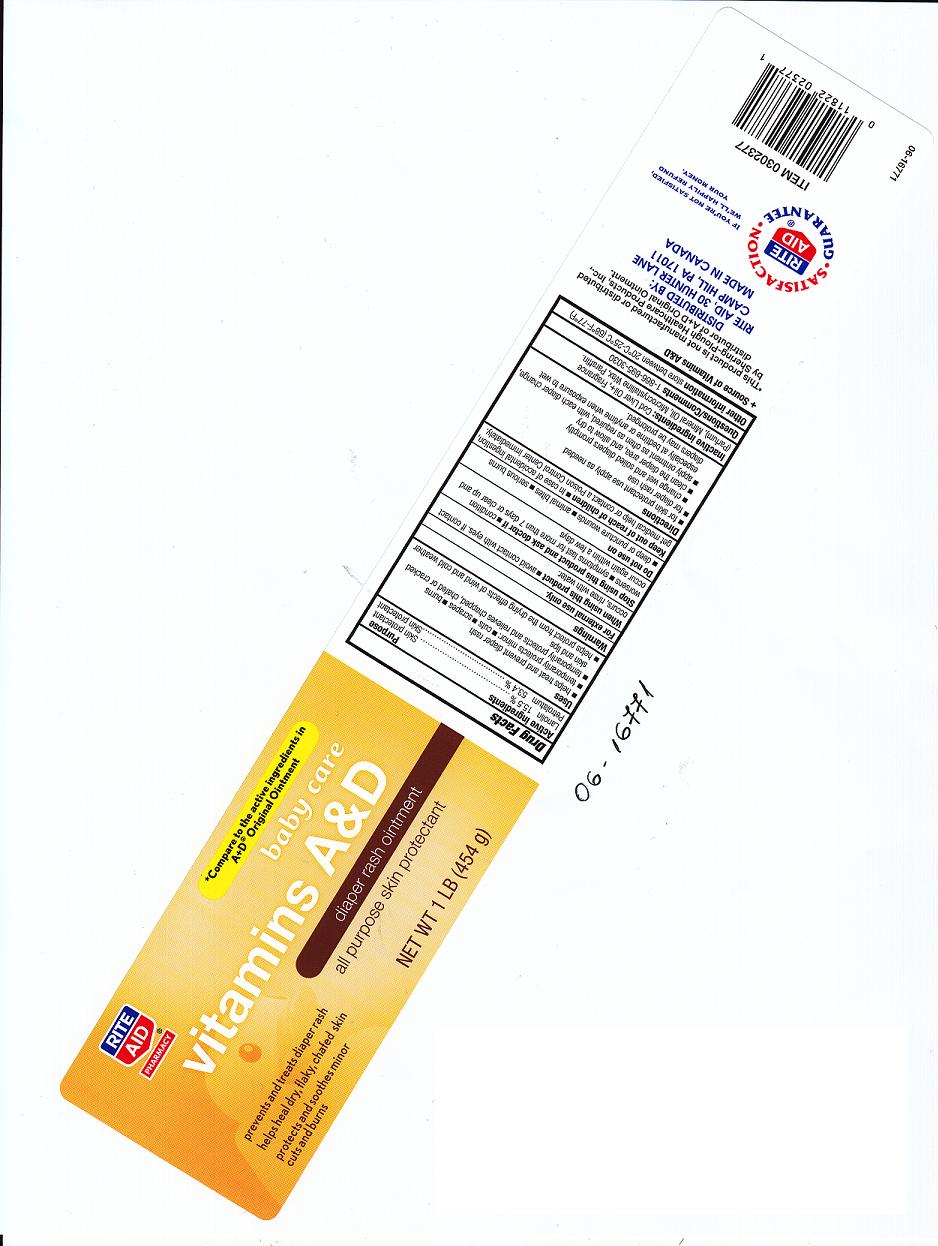 DRUG LABEL: VITAMINS A AND D DIAPER RASH 
NDC: 11822-3401 | Form: OINTMENT
Manufacturer: RITE AID
Category: otc | Type: HUMAN OTC DRUG LABEL
Date: 20110104

ACTIVE INGREDIENTS: LANOLIN 15.5 g/100 g; PETROLATUM 53.4 g/100 g
INACTIVE INGREDIENTS: COD LIVER OIL; LIGHT MINERAL OIL; MICROCRYSTALLINE WAX; PARAFFIN

DRUG FACTS

ACTIVE INGREDIENT

LANOLIN 15.5 PERCENT

PETROLATUM 53.4 PERCENT

PURPOSE

SKIN PROTECTANT

SKIN PROTECTANT

USES

HELPS TREAT AND PREVENT DIAPER RASH.

TEMPORARILY PROTECTS MINOR: CUTS SCRAPES BURNS.

TEMPORARILY PROTECTS AND RELIEVES CHAPPED, CHAFE OR CRACKED SKIN AND LIPS.

HELPS PROTECT FROM THE DRYING EFFECTS OF WIND AND COLD WEATHER.

WARNINGS

FOR EXTERNAL USE ONLY.

WHEN USING THIS PRODUCT

AVOID CONTACT WITH EYES. IF CONTACT OCCURS, RINSE WITH WATER.

STOP USING THIS PRODUCT AND ASK DOCTOR IF

CONDITION WORSENS

SYMPTOMS LAST FOR MORE THAN 7 DAYS OR CLEAR UP AND OCCUR AGAIN WITHIN A FEW DAYS

DO NOT USE ON

DEEP OR PUNCTURE WOUNDS

ANIMAL BITES

SERIOUS BURNS

KEEP OUT OF REACH OF CHILDREN

IN CASE OF ACCIDENTAL INGESTION, GET MEDICAL HELP OR CONTACT A POISON CONTROL CENTER IMMEDIATELY.

DIRECTIONS

FOR SKIN PROTECTANT USE APPLY AS NEEDED

FOR DIAPER RASH USE

CHANGE WET AND SOILED DIAPERS PROMPTLY

CLEAN THE DIAPER AREA, AND ALLOW TO DRY

APPLY OINTMENT AS OFTEN AS REQUIRED, WITH EACH DIAPER CHANGE, ESPECIALLY AT BEDTIME OR ANYTIME WHEN EXPOSURE TO WET DIAPERS MAY BE

PROLONGED.

INACTIVE INGREDIENTS

COD LIVER OIL, FRAGRANCE, LIGHT MINERAL OIL, MICROCRYSTALLINE WAX, PARAFFIN.

QUESTIONS OR COMMENTS

1-866-695-3030

OTHER INFORMATION

STORE BETWEEN 20 DEGREES CELSIUS TO 25 DEGREES CELSIUS (68 DEGREES FAHRENHEIT TO 77 DEGREES FAHRENHEIT).